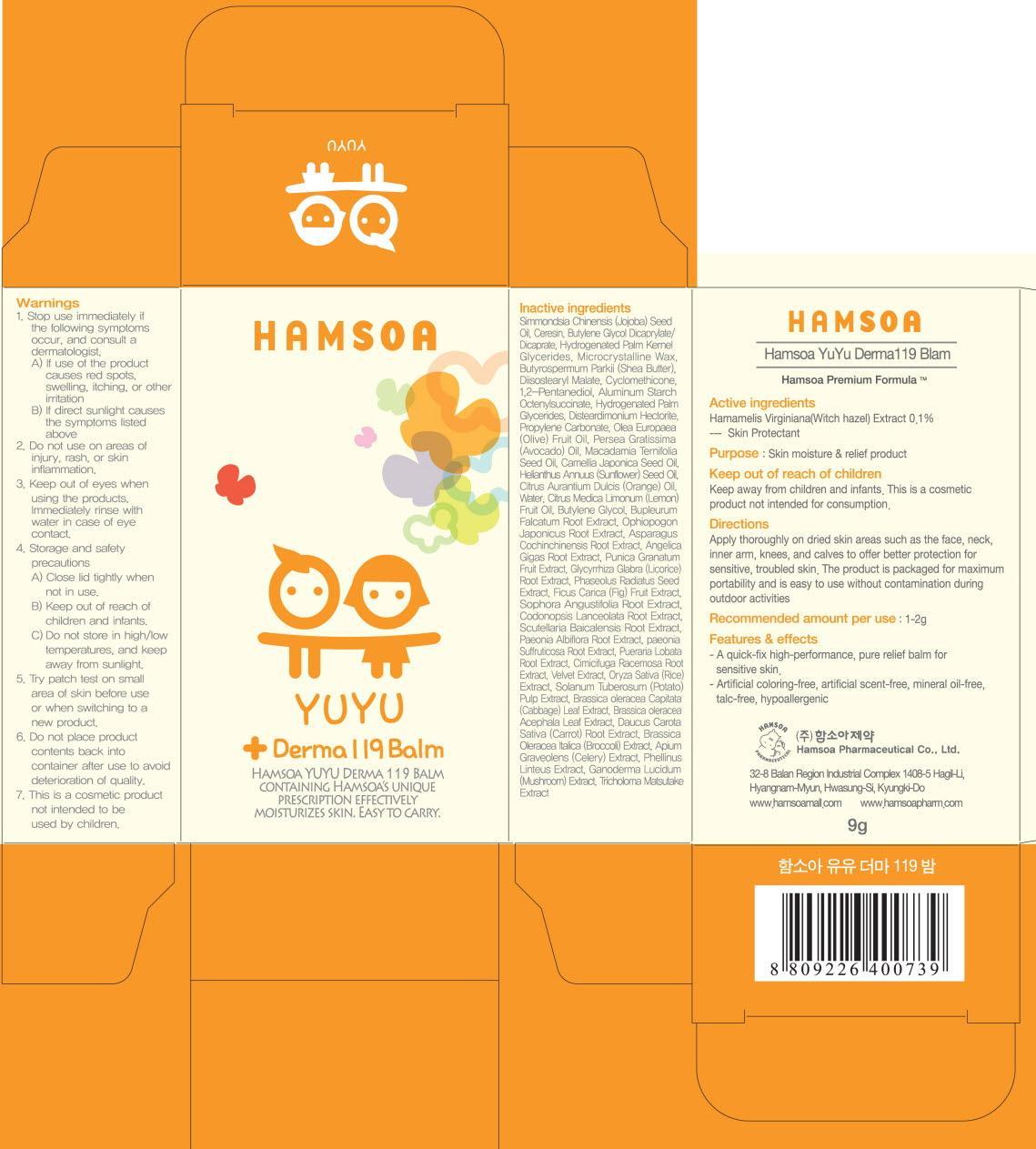 DRUG LABEL: HAMSOA YUYU DERMA119 BALM
NDC: 50964-060 | Form: CREAM
Manufacturer: HAMSOA PHARMACEUTICAL CO., LTD.
Category: otc | Type: HUMAN OTC DRUG LABEL
Date: 20120822

ACTIVE INGREDIENTS: WITCH HAZEL 0.009 g/9 g
INACTIVE INGREDIENTS: JOJOBA OIL; CERESIN; MICROCRYSTALLINE WAX; SHEA BUTTER; CYCLOMETHICONE

ACTIVE INGREDIENT

Active ingredients : Witch hazel(Hamamelis Virginiana) 0.1%

INACTIVE INGREDIENT

Inactive ingredients:
Water, Cocamidopropyl Betaine, Lauryl Glucoside, Potassium cocoyl glycinate, TEA-Cocoyl Glutamate, Cocamide Methyl MEA, Citrus Unshiu Fruit Oil, Polyquaternium-10, Polyquaternium-7, Citrus Aurantium Dulcis (Orange) Oil, Citrus Medica Limonum (Lemon) Fruit Oil, Caprylhydroxamic Acid, Caprylyl Glycol, Glycerin, Betaine, Disodium EDTA, Caramel, Glycyrrhiza Glabra (Licorice) Root Extract, Phaseolus Radiatus Seed Extract, Paeonia Albiflora Root Extract, Paeonia Suffruticosa Root Extract, Sophora Angustifolia Root Extract, Foeniculum Vulgare (Fennel) Fruit Extract, Lavandula Angustifolia (Lavender) Extract, Ocimum Basilicum (Basil) Leaf Extract,
Althaea Officinalis Root Extract, Houttuynia Cordata Extract, Anthemis Nobilis Flower Extract, Rosmarinus Officinalis (Rosemary) Leaf Extract, Panthenol, Prunus Persica (Peach) Leaf Extract, Salix Alba (Willow) Bark Extract, Morus Alba Root Extract, Broussonetia Extract, Sophora Japonica Leaf Extract, Lactobacillus Ferment, Scutellaria Baicalensis Root Extract, Camellia Sinensis Leaf Extract, Artemisia Princeps Leaf Extract, Houttuynia Cordata Extract, Citrus Junos Fruit Extract, Ricinus Communis (Castor) Seed Oil, Portulaca Oleracea Extract, Citric Acid, Squalane

PURPOSE

Purpose: Hair and body wash

WARNINGS

1. Stop use immediately if the following symptoms occur, and consult a dermatologist.
A) If use of the product causes red spots, swelling, itching, or other irritation
B) If direct sunlight causes the symptoms listed above
2. Do not use on areas of injury, rash, or skin inflammation.
3. Keep out of eyes when using the products. Immediately rinse with water in case of eye contact.
4. Thoroughly rinse with water after use on hair to avoid hair loss or bleaching.
5. Storage and safety precautions
A) Close lid tightly when not in use.
B) Keep out of reach of children and infants.
C) Do not store in high/low temperatures, and keep away from sunlight.
6. Try patch test on small area of skin before use or when switching to a new product.
7. Do not place product contents back into container after use to avoid deterioration of quality.
8. This is a cosmetic product not intended to be used by children.

INDICATIONS AND USAGE

Use an appropriate amount and lather well.
Gently massage onto body and hair, and rinse thoroughly

KEEP OUT OF REACH OF CHILDREN

DOSAGE AND ADMINISTRATION

Recommended amount per use: 1-2g